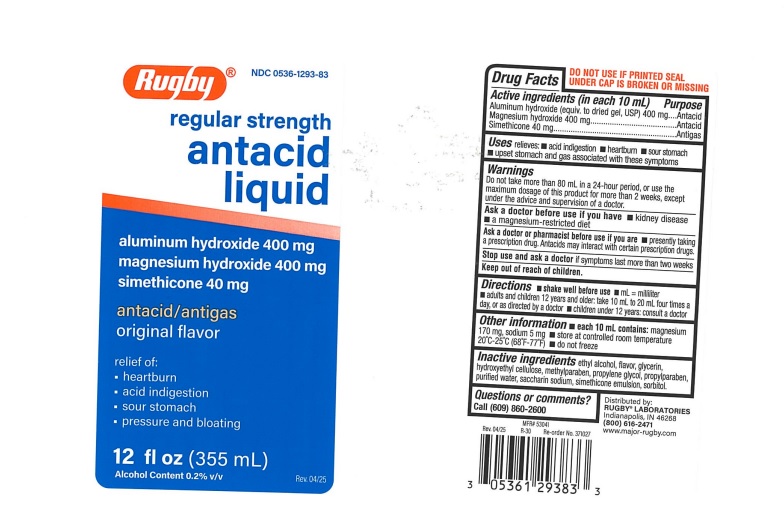 DRUG LABEL: Antacid
NDC: 0536-1293 | Form: LIQUID
Manufacturer: Rugby Laboratories
Category: otc | Type: Human OTC Drug Label
Date: 20251124

ACTIVE INGREDIENTS: ALUMINUM HYDROXIDE 400 mg/10 mL; MAGNESIUM HYDROXIDE 400 mg/10 mL; DIMETHICONE 40 mg/10 mL
INACTIVE INGREDIENTS: ALCOHOL; GLYCERIN; HYDROXYETHYL CELLULOSE, UNSPECIFIED; METHYLPARABEN; PROPYLENE GLYCOL; PROPYLPARABEN; WATER; SACCHARIN SODIUM; SORBITOL; SILICON DIOXIDE

Rugby Regular Strength Antacid Liquid

ACTIVE INGREDIENTS (in each 10 mL)

Aluminum hydroxide (equiv. to dried gel, USP) 400 mg
Magnesium hydroxide 400 mg
Simethicone 40 mg

PURPOSE

Antacid
Antacid
Antigas

USE(S)

relieves:

- acid indigestion
- heartburn
- sour stomach
- upset stomach and gas associated with these symptoms

WARNINGS

Do not take more than 80 mL in a 24-hour period, or use the maximum dosage of this product for more than 2 weeks, except under the advice and supervision of a doctor.

ASK A DOCTOR BEFORE USE IF YOU HAVE

- kidney disease
- a magnesium-restricted diet

ASK A DOCTOR OR PHARMACIST BEFORE USE IF YOU ARE

- presently taking a prescription drug. Antacids may interact with certain prescription drugs.

STOP USE AND ASK DOCTOR

if symptoms last more than two weeks

KEEP OUT OF REACH OF CHILDREN

.

DIRECTIONS

- shake well before use
- mL = milliliter
- adults and children 12 years and older: take 10 mL to 20 mL four times a day, or as directed by a doctor
- children under 12 years: consult a doctor

OTHER INFORMATION

- each 10 mL contains: magnesium 170 mg, sodium 5 mg
- store at controlled room temperature 20ºC-25ºC (68º-77ºF)
- do not freeze

INACTIVE INGREDIENTS

ethyl alcohol, flavor, glycerin, hydroxyethyl cellulose, methylparaben, propylene glycol, propylparaben, purified water, saccharin sodium, simethicone emulsion, sorbitol

PRINCIPAL DISPLAY PANEL

Rugby

NDC 0536-1293-83
regular strength
antacid liquid
aluminum hydroxide, 400 mg
magnesium hydroxide, 400 mg
simethicone, 40 mg

antacid and antigas
original flavor

Relief of:

- heartburn
- acid indigestion
- sour stomach
- pressure & bloating

12 FL OZ (355 mL)
Alcohol content 0.2% v/v